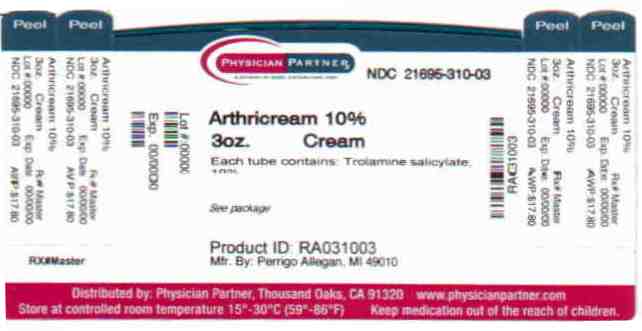 DRUG LABEL: Arthricream
NDC: 21695-310 | Form: CREAM
Manufacturer: Rebel Distributors Corp
Category: otc | Type: HUMAN OTC DRUG LABEL
Date: 20110209

ACTIVE INGREDIENTS: TROLAMINE SALICYLATE 10 g/100 g
INACTIVE INGREDIENTS: ALOE VERA LEAF; DIMETHICONE; EDETATE DISODIUM; GLYCERYL MONOSTEARATE; METHYLPARABEN; PROPYLENE GLYCOL; PROPYLPARABEN; WATER; SORBITOL

Perrigo Arthricream Rub Drug Facts

Active ingredient

Trolamine salicylate 10%

Purpose

Topical analgesic

Uses

temporarily relieves minor aches and pains of muscles and joints associated with:

- arthritis
- simple backache
- strains
- sprains
- bruises

Warnings

For external use only

When using this product

- use only as directed
- do not bandage tightly or use with a heating pad
- avoid contact with the eyes or mucous membranes
- do not apply to wounds or damaged skin

Stop use and ask a doctor if

- condition worsens
- symptoms persist for more than 7 days or clear up and occur again within a few days
- redness is present
- irritation develops

If pregnant or breast-feeding,

ask a health professional before use.

Keep out of reach of children.

If swallowed, get medical help or contact a Poison Control Center right away.

Directions

adults and children over 12 years:

- apply generously to affected area
- massage into painful area until thoroughly absorbed into skin
- repeat as necessary, but not more than 4 times daily

children 12 years or younger: ask a doctor

Other information

- store at 20°-25°C (68°-77°F)

Inactive ingredients

aloe barbadensis leaf juice, dimethicone, edetate disodium, glyceryl monostearate, methylparaben, PEG-100 stearate, propylene glycol, propylparaben, purified water, sorbitol solution

Questions or comments?

1-800-719-9260

Repackaged by:

Rebel Distributors Corp

Thousand Oaks, CA 91320

Principal Display Panel

Compare to Aspercreme® active ingredient

Pain Relieving Cream

Arthricream Rub

Trolamine salicylate, 10%

with aloe